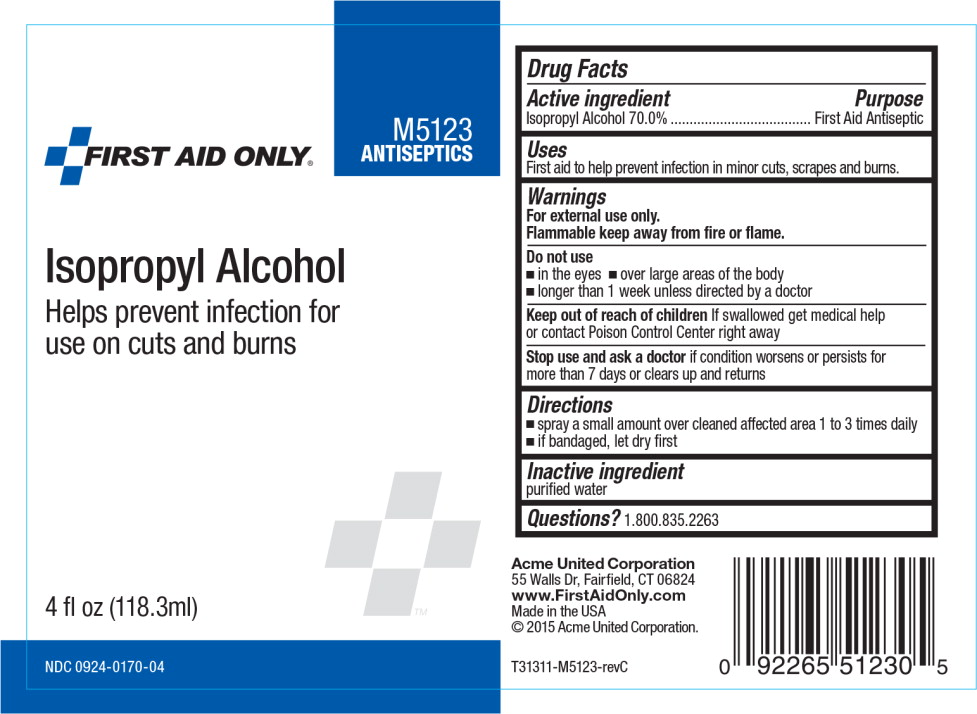 DRUG LABEL: First Aid Only Isopropyl Alcohol

NDC: 0924-0170 | Form: SPRAY
Manufacturer: Acme United Corp.

Category: otc | Type: HUMAN OTC DRUG LABEL
Date: 20160205

ACTIVE INGREDIENTS: Isopropyl Alcohol
 700 mL/1 L
INACTIVE INGREDIENTS: water

Drug Facts

Active ingredient

Isopropyl Alcohol 70.0%

Purpose

First Aid Antiseptic

Uses

First aid to help prevent infection in minor cuts, scrapes and burns.

Warnings

For external use only.

Flammable keep away from fire or flame.

Do not use

- in the eyes
- over larger areas of the body
- longer than 1 week unless directed by a doctor

Keep out of reach of children If swallowed get medical help or contact Poison Control Center right away

Stop use and ask a doctor

- in case of deep puncture wounds, animal bites, or serious burns
- if condition persists or gets worse

Directions

- spray a small amount over cleaned affected area 1 to 3 times daily
- if bandaged, let dry first

Inactive ingredient

purified water

Principal Display Panel - Bottle Label

FIRST AID ONLY®

M5123

ANTISEPTICS

Isopropyl Alcohol

Helps prevent infection for
use on cuts and burns

4 fl oz (118.3ml)

NDC 0924-0170-04